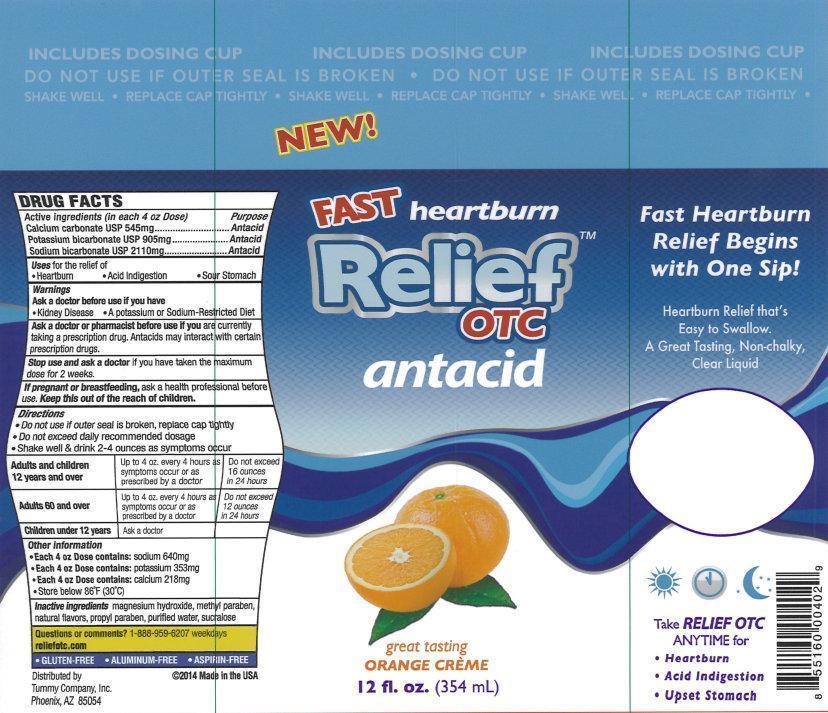 DRUG LABEL: Relief OTC antacid
NDC: 69016-001 | Form: LIQUID
Manufacturer: Tummy Company, Inc.
Category: otc | Type: HUMAN OTC DRUG LABEL
Date: 20140529

ACTIVE INGREDIENTS: CALCIUM CARBONATE 545 mg/118 mL; POTASSIUM BICARBONATE 905 mg/118 mL; SODIUM BICARBONATE 2110 mg/118 mL
INACTIVE INGREDIENTS: MAGNESIUM HYDROXIDE; METHYLPARABEN; PROPYLPARABEN; WATER; SUCRALOSE

Relief OTC Antacid

Active ingredients (in each 4 oz Dose)

Calcium carbonate USP 545mg

Potassium bicarbonate USP 905mg

Sodium bicarbonate USP 2110mg

Purpose

Antacid

Antacid

Antacid

Uses

for the relief of

• Heartburn • Acid Indigestion • Sour Stomach

Warnings

Ask a doctor before use if you have

•Kidney Disease

•A Potassium or Sodium-Restricted Diet

Ask a doctor or pharmacist before use if you

are currently taking a prescription drug. Antacids may interact with certain prescription drugs.

Stop Use and ask a doctor

if you have taken the maximum dose for 2 weeks.

If pregnant or breastfeeding,

ask a health professional before use.

Directions

- Do not use if outer seal is broken, replace cap tightly
- Do not exceed daily recommended dosage
- Shake well & drink 2-4 ounces as symptoms occur

Adults and children 12 years and over | Up to 4oz. every 4 hours as sumptoms occur or as prescribed by a doctor | Do not exceed 16 ounces in 24 hours
Adults 60 and over | Up to 4oz. every 4 hours as sumptoms occur or as prescribed by a doctor | Do not exceed 12 ounces in 24 hours
Children under 12 years | Ask a doctor

Other information

- Each 4 oz Dose contains: sodium 640mg
- Each 4 oz Dose contains: potassium 353mg
- Each 4 oz Dose contains: calcium 218mg
- Store below 86 degrees F (30 degrees C)

Inactive ingredients

magnesium hydroxide, metyl paraben, natural flavors, propyl paraben, purified water, sucralose

Questions or comments?

1-888-959-6207 weekdays

reliefotc.com

Representative Label

New!

Fast heartburn Relief

OTC

antacid

great tasting

ORANGE CREME

12 fl. oz. (354 mL)

Fast Heartburn Relief Begins with One Sip!

Heartburn Relief that's Easy to Swallow.

A Great Tasting, Non-Chalky, Clear Liquid

Take RELIEF OTC ANYTIME for

- Hearburn
- Acid Indigestion
- Upset Stomach

- GLUTEN-FREE
- ALUMINUM-FREE
- ASPIRIN-FREE

Distributed by

Tummy Company, Inc.

Phoenix,

AZ 85054

2014 Made in the USA